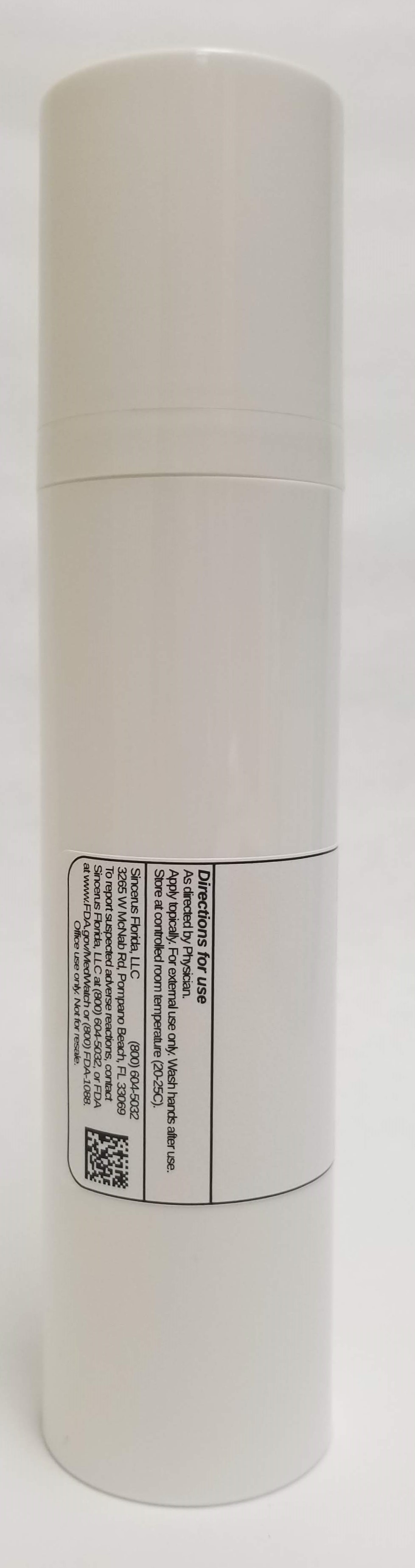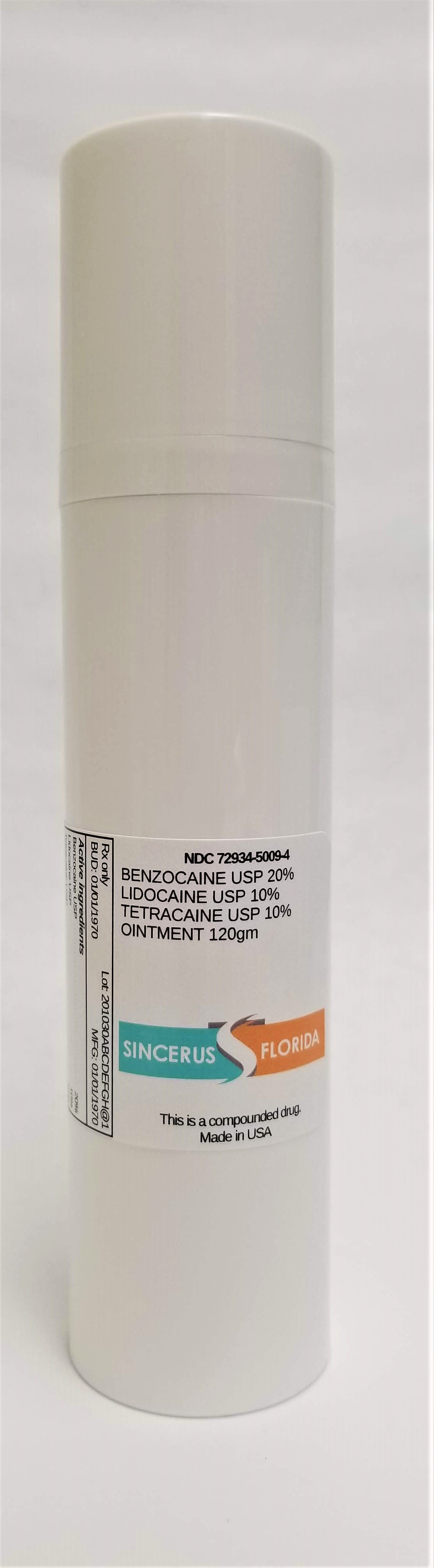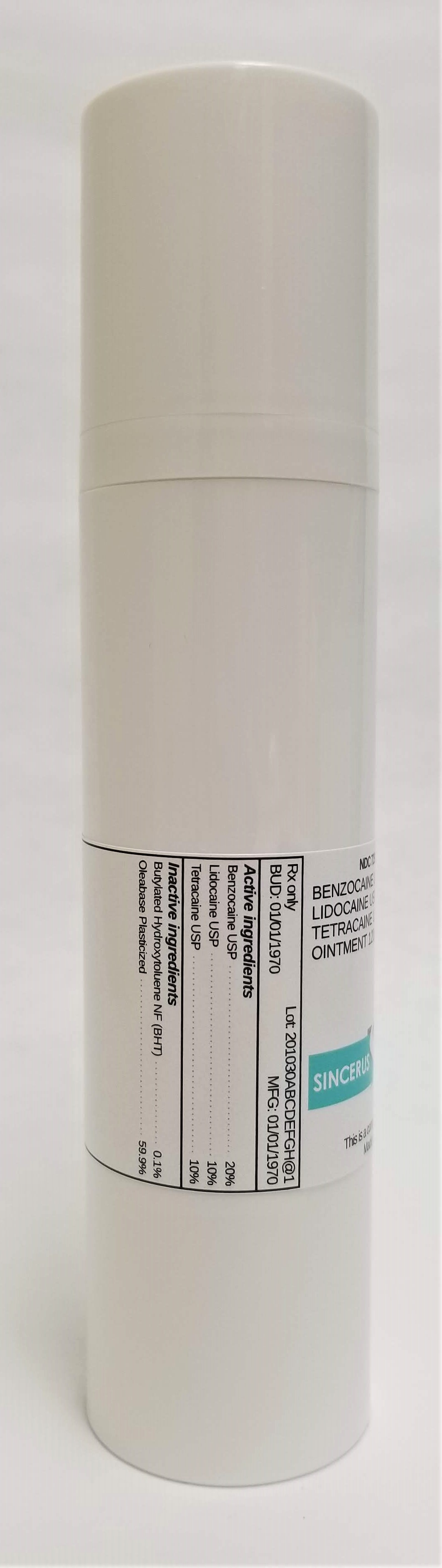 DRUG LABEL: BENZOCAINE 20% / LIDOCAINE 10% / TETRACAINE 10%
NDC: 72934-5009 | Form: OINTMENT
Manufacturer: Sincerus Florida, LLC
Category: prescription | Type: HUMAN PRESCRIPTION DRUG LABEL
Date: 20190517

ACTIVE INGREDIENTS: BENZOCAINE 20 g/100 g; LIDOCAINE 10 g/100 g; TETRACAINE 10 g/100 g

BENZOCAINE 20% / LIDOCAINE 10% / TETRACAINE 10%